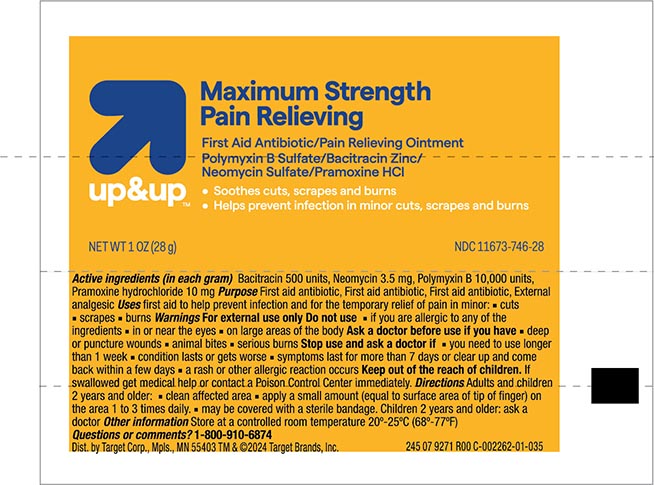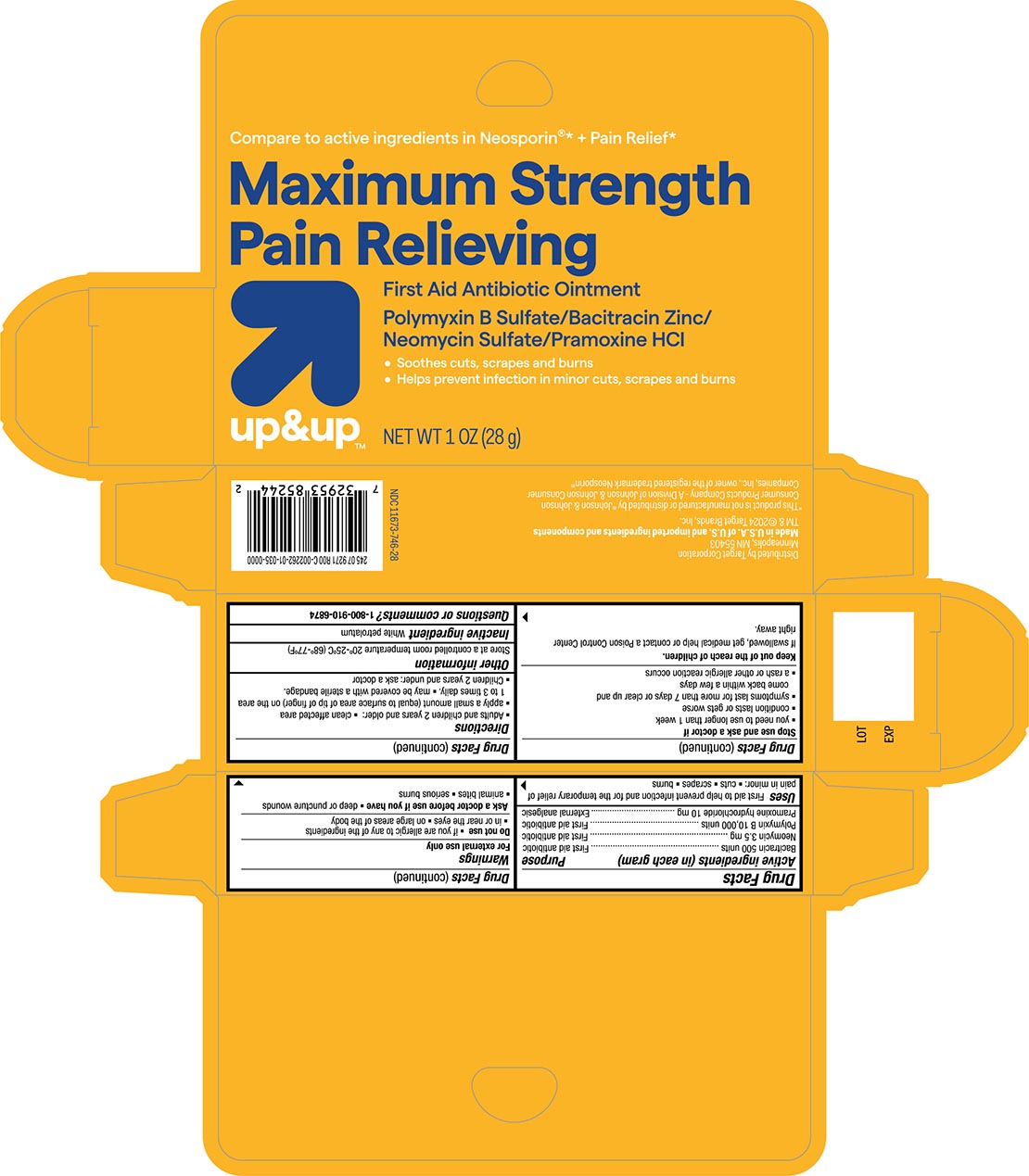 DRUG LABEL: Triple Antibiotic and Pain Relief
NDC: 11673-746 | Form: OINTMENT
Manufacturer: Target Corporation
Category: otc | Type: HUMAN OTC DRUG LABEL
Date: 20240117

ACTIVE INGREDIENTS: BACITRACIN ZINC 500 [USP'U]/1 g; POLYMYXIN B SULFATE 10000 [USP'U]/1 g; NEOMYCIN SULFATE 3.5 mg/1 g; PRAMOXINE HYDROCHLORIDE 10 mg/1 g
INACTIVE INGREDIENTS: PETROLATUM

Target Up &Up Maximum Strength Triple Antibiotic+Pain Relief

Active ingredients (in each gram)

Bacitracin 500

Neomycin 3.5 mg

Polymyxin B 10,000 units

Pramoxine HCL 10 mg

Purpose

First aid antibiotic

First aid antibiotic

First aid antibiotic

Pain Relief

Uses

helps prevent infection in and temporarily relieves pain due to minor:

- cuts
- scrapes
- burns

Warnings For external use only

Do not use

- do not use if you are allergic to any of the ingredients
- or near the eyes
- or on large areas of the body

Ask a doctor before use if you have

- deep or puncture wounds
- animal bites
- serious burns

Stop use and ask a doctor if

- you need to use longer than 1 week
- condition persists or gets worse
- symptoms last for more than 7 days or clear up and come back within a few days
- a rash or other allergic reaction develops

KEEP OUT OF REACH OF CHILDREN

Keep out of the reach of children. If swallowed get medical help or contact a Poison Control Center immediately.

Directions

- clean the affected area
- apply a small amount (equal to surface area of tip of finger) on the area 1 to 3 times daily.
- may be covered with a sterile bandage

Other information

Store at a controlled room temperature 68º-77ºF (20º-25ºC)

Inactive ingredient

Petrolatum

Principal Display panel

Target Up & Up NDC 11673-746-28

Maximum Strength Pain Relieving

First aid Antibiotic Ointment

Polymixin B Sulfate/Bacitracin Zinc/Neomycin Sulfate/ Pramoxine HCl

NET WT 1.0 OZ (28g)